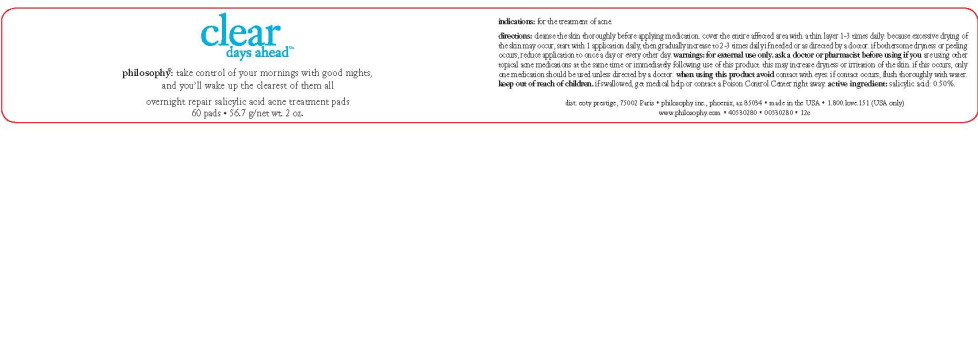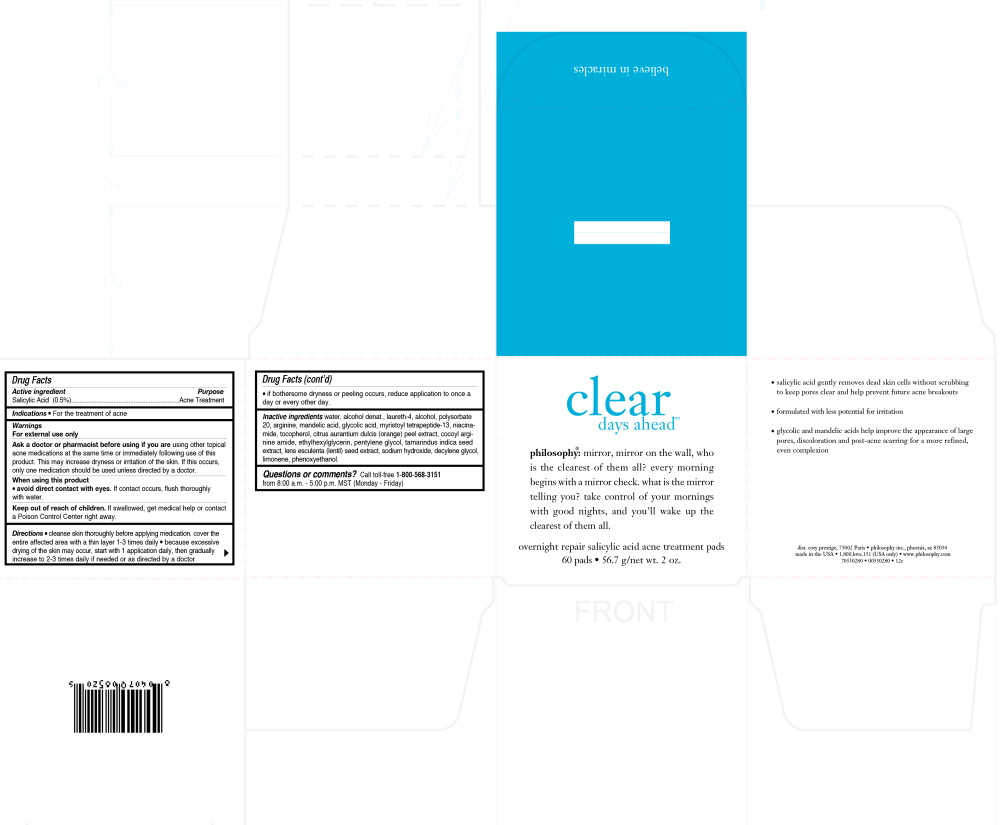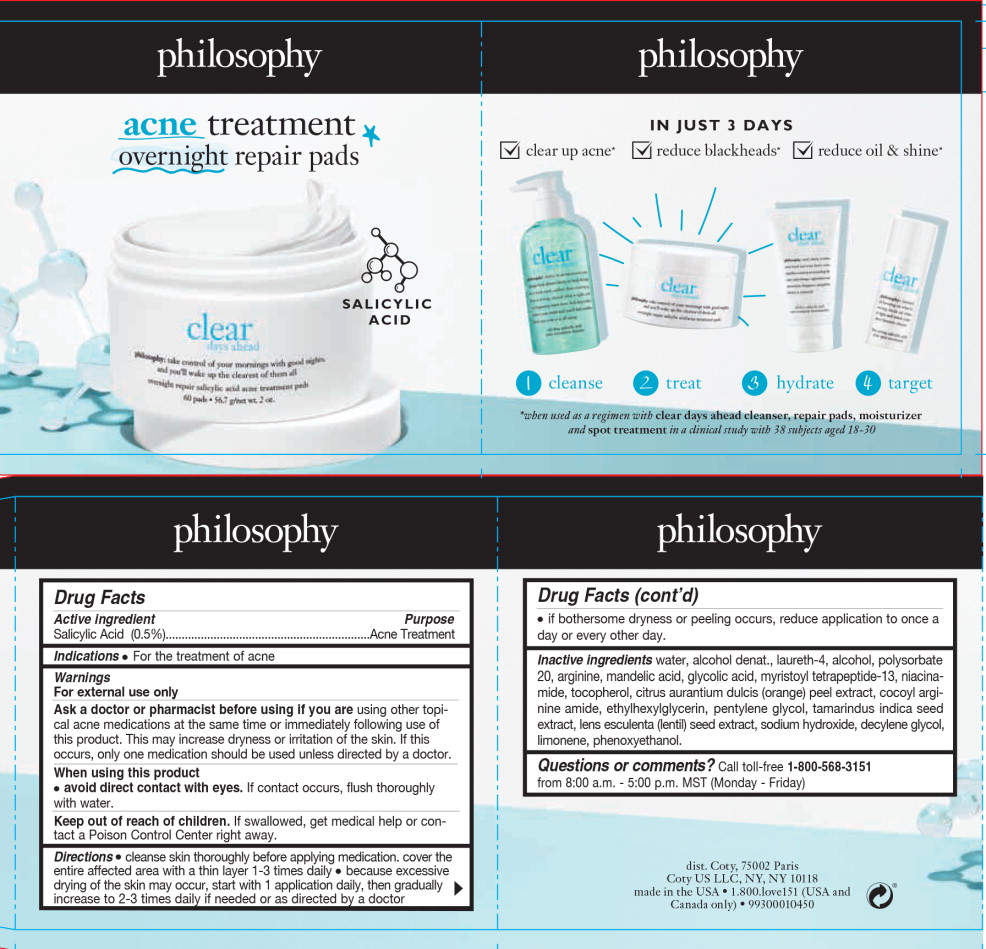 DRUG LABEL: clear days ahead
NDC: 50184-1015 | Form: CLOTH
Manufacturer: Philosophy Inc.
Category: otc | Type: HUMAN OTC DRUG LABEL
Date: 20251217

ACTIVE INGREDIENTS: SALICYLIC ACID 283.5 mg/56.7 g
INACTIVE INGREDIENTS: WATER; LAURETH-4; ALCOHOL; POLYSORBATE 20; ARGININE; MANDELIC ACID; NIACINAMIDE; TOCOPHEROL; ORANGE PEEL; ETHYLHEXYLGLYCERIN; PENTYLENE GLYCOL; TAMARIND SEED; LENTIL; SODIUM HYDROXIDE; DECYLENE GLYCOL; PHENOXYETHANOL

Drug Facts

Active ingredient

Salicylic Acid (0.5%)

Purpose

Acne Treatment

Indications

- For the treatment of acne

Warnings

For external use only

Ask a doctor or pharmacist before using if you are using other topical acne medications at the same time or immediately following use of this product. This may increase dryness or irritation of the skin. If this occurs, only one medication should be used unless directed by a doctor.

When using this product

- avoid direct contact with eyes. If contact occurs, flush thoroughly with water.

Keep out of reach of children. If swallowed, get medical help or contact a Poison Control enter right away.

Directions

- cleanse skin thoroughly before applying medication. cover the entire affected area with a thin layer 1-3 times daily
- because excessive drying of the skin may occur, start with 1 application daily, then gradually increase to 2-3 times daily if needed or as directed by a doctor
- if bothersome dryness or peeling occurs, reduce application to once a day or every other day.

Inactive ingredients

water, alcohol denat., laureth-4, alcohol, polysorbate 20, arginine, andelic acid, glycolic acid, myristoyl tetrapeptide-13, niacinamide, tocopherol, citrus aurantium dulcis (orange) peel extract, cocoyl arginine amide, ethylhexylglycerin, pentylene glycol, tamarindus indica seed extract, lens esculenta (lentil) seed extract, sodium hydroxide, decylene glycol, limonene, phenoxyethanol.

Questions or comments?

Call toll-free 1-800-568-3151 from 8:00 a.m. - 5:00 p.m. MST (Monday - Friday)

Principal Display Panel – 56.7 g Sleeve Label

philosophy

acne treatment

overnight repair pads

salicylic acid

Principal Display Panel - 56.7 g Box Label

clear

days ahead™

philosophy®: mirror, mirror on the wall, who
is the clearest of them all? every morning
begins with a mirror check. what is the mirror
telling you? take control of your mornings
with good nights, and you'll wake up the
clearest of them all.

overnight repair salicylic acid acne treatment pads

60 pads • 56.7 g/net wt. 2 oz.

Principal Display Panel - 56.7 g Bottle Label

clear

days ahead™

philosophy®: take control of your mornings with good nights,
and you'll wake up the clearest of them all

overnight repair salicylic acid acne treatment pads

60 pads • 56.7 g/net wt. 2 oz.